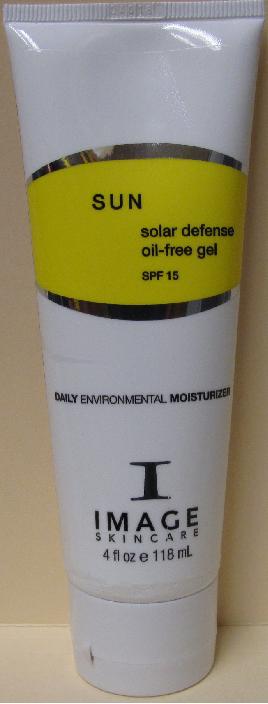 DRUG LABEL: SUN Solar Defense Oil-free Gel SPF 15
NDC: 62742-4039 | Form: CREAM
Manufacturer: Allure Labs, Inc.
Category: otc | Type: HUMAN OTC DRUG LABEL
Date: 20100701

ACTIVE INGREDIENTS: TITANIUM DIOXIDE 16 mg/1 mL; OCTINOXATE 75 mg/1 mL; OXYBENZONE 30 mg/1 mL

Drug Facts

Active Ingredients:

Titanium Dioxide 1.6%

Ethylhexyl Methoxycinnamate (Octinoxate) 7.50%

Benzophenone-3: 3.00%

Purpose:

Sunscreen

Uses:

- An oil-free UVA/UVB broad spectrum daily moisturizer. Provides ultimate protection against the aging effects of the sun and other environmental exposure. Enriched with essential vitamins and anti-oxidants that prevent free radical damage and preserving skin hydration for the entire day.
- Water-resistant
- Paraben-free

Directions:
Apply liberally 15-30 minute prior to sun exposure. Reapply after prolonged swimming or vigorous activity.
Indications:
Universal for all skin types.

Warnings:

For external use only.

When using this product

- Keep out of eyes. If contact occurs rinse with water.
- Discontinue use if irritation or redness occurs.

Keep out of reach of children

Inactive Ingredients:
Water (Aqua), Ethylhexyl Methoxycinnamate, Ascorbyl Palmitate, Cyclomethicone, Benzophenone-3, Glycerin, Glyceryl Stearate, Camellia Sinensis Leaf Extract (Green Tea), Tocopheryl Acetate, Phenoxyethanol, Lecithin, C13-14 Isoparaffin Citrus blend, Xanthan Gum, Disodium EDTA.

PACKAGE LABEL

Distributor:
Image International
Palm Beach, FL 33411 USA
Image of the product:
Sun Solar Defense Oil-free Gel SPF 15